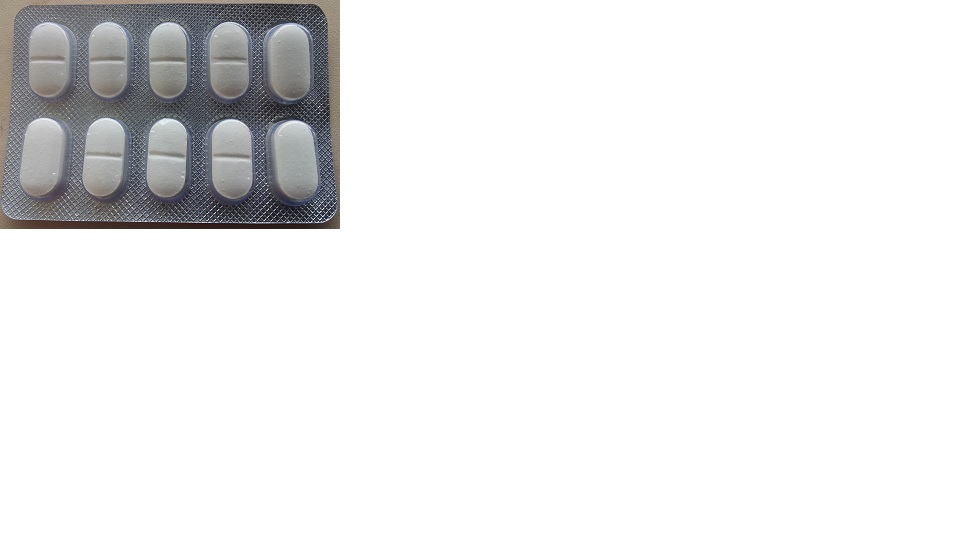 DRUG LABEL: IBUPROFEN COLD AND SINUS
NDC: 46084-091 | Form: TABLET, COATED
Manufacturer: A P J Laboratories Limited
Category: otc | Type: HUMAN OTC DRUG LABEL
Date: 20130429

ACTIVE INGREDIENTS: IBUPROFEN 200 mg/1 1; PSEUDOEPHEDRINE HYDROCHLORIDE 30 mg/1 1
INACTIVE INGREDIENTS: CALCIUM CARBONATE 20 mg/1 1; STARCH, CORN 8 mg/1 1; METHYLPARABEN .5 mg/1 1; PROPYLPARABEN .2 mg/1 1; SODIUM STARCH GLYCOLATE TYPE A POTATO 6 mg/1 1; TALC 4 mg/1 1; MAGNESIUM STEARATE 3 mg/1 1; SILICON DIOXIDE 1 mg/1 1; CROSCARMELLOSE SODIUM 1.5 mg/1 1; SODIUM LAURYL SULFATE 1 mg/1 1; ISOPROPYL ALCOHOL 60 mg/1 1; METHYLENE CHLORIDE 150 mg/1 1; TITANIUM DIOXIDE 1.5 mg/1 1

ACTIVE INGREDIENT

IBUPROFEN

PSEUDOEPHEDRINE HYDROCHLORIDE

PURPOSE

Pain reliever/Fever reducer

Nasal decongestant

KEEP OUT OF REACH OF CHILDREN

In case of overdose, get medical help or contact a Poison Control Center right away. (1-800-222-1222).

uses

temporarily relieves these symptoms associated with the common cold or flu:

•fever

•sinus pressure

•nasal congestion

•headache

•minor body aches and pains

Allergy alert: Ibuprofen may cause a severe allergic reaction, especially in people allergic to aspirin. Symptoms may include:

•hives

•facial swelling

•asthma (wheezing)

•shock

•skin reddening

•rash

•blisters

If an allergic reaction occurs, stop use and seek medical help right away.

Stomach bleeding warning: This product contains an NSAID, which may cause severe stomach bleeding. The chance is higher if you:

•are age 60 or older

•have had stomach ulcers or bleeding problems

•take a blood thinning (anticoagulant) or steroid drug

•take other drugs containing prescription or nonprescription NSAIDs, [aspirin, ibuprofen, naproxen, or others]

•have 3 or more alcoholic drinks every day while using this product

•take more or for a longer time than directed

DOSAGE AND ADMINISTRATION

•do not take more than directed

•the smallest effective dose should be used.

•adults and children 12 years of age and over:

•take 1 caplet every 4 to 6 hours while symptoms persist. If symptoms do not respond to 1 caplet, 2 caplets may be used.

•do not use more than 6 caplets in any 24-hour period unless directed by a doctor.

•children under 12 years of age: do not use.

DO NOT USE

if you have ever had an allergic reaction to any other pain reliever/fever reducer

•if you are now taking a prescription monoamine oxidase inhibitor (MAOI) (certain drugs for depression, psychiatric, or emotional conditions, or Parkinson’s disease), or for 2 weeks after stopping the MAOI drug. If you do not know if your prescription drug contains an MAOI, ask a doctor or pharmacist before taking this product.

•in children under 12 years of age

•right before or after heart surgery

INACTIVE INGREDIENT

•CALCIUM CARBONATE

•STARCH, CORN

•METHYLPARABEN

•PROPYLPARABEN

•SODIUM STARCH GLYCOLATE TYPE A POTATO

•TALC

•MAGNESIUM STEARATE

•SILICON DIOXIDE

•CROSCARMELLOSE SODIUM

•SODIUM LAURYL SULFATE

•ISOPROPYL ALCOHOL

•METHYLENE CHLORIDE

•TITANIUM DIOXIDE